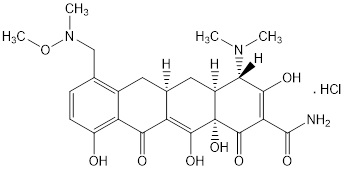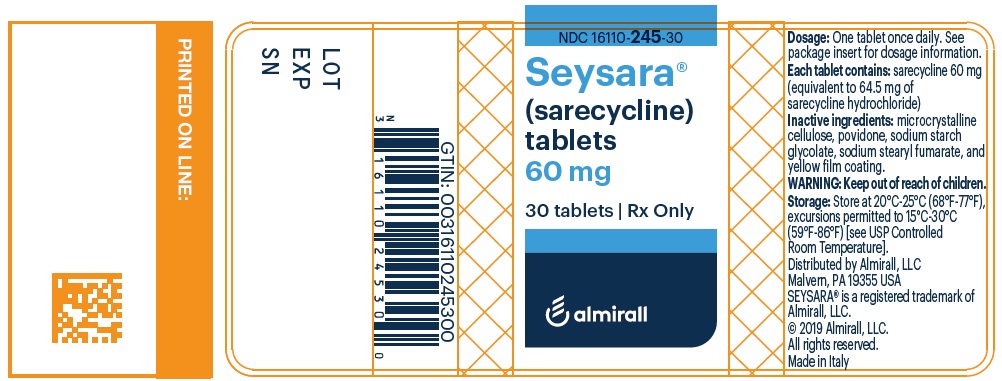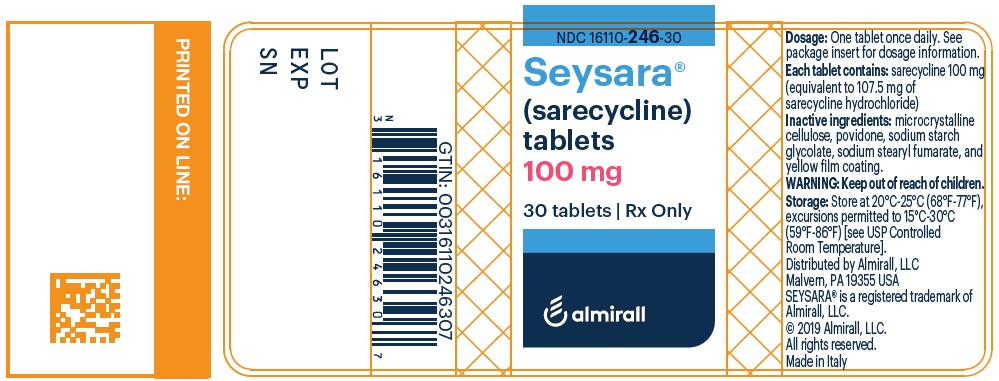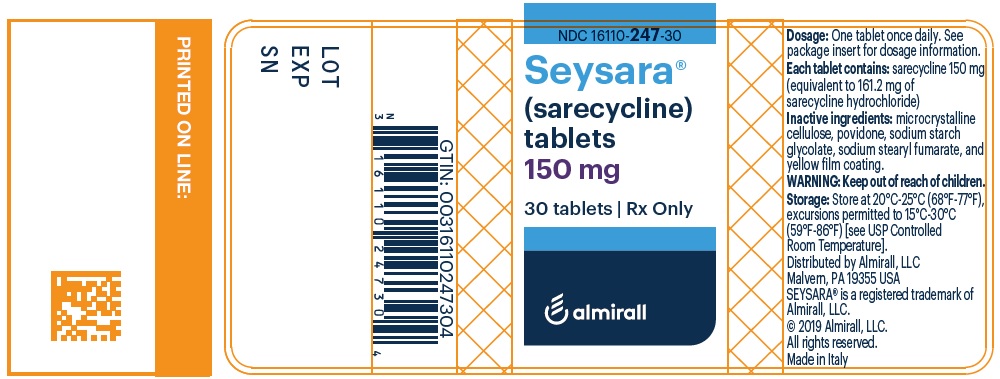 DRUG LABEL: Seysara
NDC: 16110-245 | Form: TABLET, COATED
Manufacturer: Almirall, LLC
Category: prescription | Type: HUMAN PRESCRIPTION DRUG LABEL
Date: 20240605

ACTIVE INGREDIENTS: SARECYCLINE HYDROCHLORIDE 60 mg/1 1
INACTIVE INGREDIENTS: MICROCRYSTALLINE CELLULOSE; POVIDONE, UNSPECIFIED; SODIUM STARCH GLYCOLATE TYPE A POTATO; SODIUM STEARYL FUMARATE; D&C YELLOW NO. 10; FERRIC OXIDE YELLOW; METHACRYLIC ACID - ETHYL ACRYLATE COPOLYMER (1:1) TYPE A; POLYETHYLENE GLYCOL, UNSPECIFIED;  POLYVINYL ALCOHOL, UNSPECIFIED; SODIUM BICARBONATE; TALC; TITANIUM DIOXIDE

HIGHLIGHTS OF PRESCRIBING INFORMATION

These highlights do not include all the information needed to use SEYSARA® safely and effectively. See full prescribing information for SEYSARA®.
SEYSARA® (sarecycline) tablets for oral use.
Initial U.S. Approval: 2018

1 INDICATIONS AND USAGE

SEYSARA® is a tetracycline-class drug indicated for the treatment of inflammatory lesions of non-nodular moderate to severe acne vulgaris in patients 9 years of age and older. (1)

Limitations of Use
Efficacy of SEYSARA beyond 12 weeks and safety beyond 12 months have not been established. SEYSARA has not been evaluated in the treatment of infections. To reduce the development of drug-resistant bacteria as well as to maintain the effectiveness of other antibacterial drugs, SEYSARA should be used only as indicated [see Warnings and Precautions (5.6)].

2 DOSAGE AND ADMINISTRATION

The recommended dosage of SEYSARA is once daily with or without food (2):

- 60 mg for patients who weigh 33-54 kg,
- 100 mg for patients who weigh 55-84 kg,
- 150 mg for patients who weigh 85-136 kg.

3 DOSAGE FORMS AND STRENGTHS

Tablets: 60 mg, 100 mg, 150 mg (3)

4 CONTRAINDICATIONS

SEYSARA is contraindicated in persons who have shown hypersensitivity to any of the tetracyclines. (4)

5 WARNINGS AND PRECAUTIONS

- The use of SEYSARA during tooth development (second and third trimesters of pregnancy, infancy, and childhood up to the age of 8 years) may cause permanent discoloration of the teeth (yellow-gray-brown). (5.1)
- If Clostridium difficile Associated Diarrhea (antibiotic associated colitis) occurs, discontinue SEYSARA. (5.2)
- Central nervous system side effects, including light-headedness, dizziness or vertigo, have been reported with tetracycline use. Patients who experience these symptoms should be cautioned about driving vehicles or using hazardous machinery. These symptoms may disappear during therapy and may disappear when the drug is discontinued. (5.3)
- SEYSARA may cause intracranial hypertension. Discontinue SEYSARA if symptoms occur. (5.4)
- Photosensitivity can occur with SEYSARA. Patients should minimize or avoid exposure to natural or artificial sunlight. (5.5)

6 ADVERSE REACTIONS

Most common adverse reaction (incidence ≥ 1%) is nausea. (6.1)

To report SUSPECTED ADVERSE REACTIONS, contact Almirall at 1-866-665-2782 or FDA at 1-800-FDA-1088 or www.fda.gov/medwatch.

7 DRUG INTERACTIONS

- Oral retinoids: avoid coadministration. (5.4, 7.1)
- Antacids and iron preparations: separate dosing of SEYSARA. (7.1)
- Penicillin: avoid coadministration. (7.2)
- Anticoagulants: decrease anticoagulant dosage as appropriate. (7.2)
- P-glycoprotein substrates: monitor for toxicities of drugs that may require dosage reduction. (7.2)

8 USE IN SPECIFIC POPULATIONS

- Sarecycline, like other tetracycline-class drugs, can cause fetal harm when administered to a pregnant woman. (5.1, 8.1)
- The use of drugs of the tetracycline class during tooth development may cause permanent discoloration of teeth. (5.1, 8.4)
- Lactation: Breastfeeding is not recommended. (8.2)

FULL PRESCRIBING INFORMATION

1 INDICATIONS AND USAGE

SEYSARA® (sarecycline) tablet, is indicated for the treatment of inflammatory lesions of non-nodular moderate to severe acne vulgaris in patients 9 years of age and older.

Limitations of Use
Efficacy of SEYSARA beyond 12 weeks and safety beyond 12 months have not been established. SEYSARA has not been evaluated in the treatment of infections [see Clinical Studies (14)].

To reduce the development of drug-resistant bacteria as well as to maintain the effectiveness of other antibacterial drugs, SEYSARA should be used only as indicated [see Warnings and Precautions (5.6)].

2 DOSAGE AND ADMINISTRATION

The recommended dosage of SEYSARA is based on body weight described in Table 1. If there is no improvement after 12 weeks, reassess treatment with SEYSARA.

Table 1: Dosing Table for SEYSARA
Body Weight (kg) | Tablet Strength
33 to 54 kg | 60 mg tablet
55 to 84 kg | 100 mg tablet
85 to 136 kg | 150 mg tablet

Take SEYSARA once daily, with or without food. To reduce the risk of esophageal irritation and ulceration, administer SEYSARA with adequate amounts of fluid.

3 DOSAGE FORMS AND STRENGTHS

SEYSARA (sarecycline) tablets:

1. 60 mg: capsule-shaped, yellow, film-coated tablets debossed with “S60” on one side and blank on the other side.
2. 100 mg: capsule-shaped, yellow, film-coated tablets debossed with “S100” on one side and blank on the other side.
3. 150 mg: capsule-shaped, yellow, film-coated tablets debossed with “S150” on one side and blank on the other side.

4 CONTRAINDICATIONS

SEYSARA is contraindicated in persons who have shown hypersensitivity to any of the tetracyclines.

5 WARNINGS AND PRECAUTIONS

5.1 Teratogenic Effects

SEYSARA, like other tetracyclines, can cause fetal harm when administered to a pregnant woman. If SEYSARA is used during pregnancy or if the patient becomes pregnant while taking SEYSARA, the patient should be informed of the potential hazard to the fetus and treatment should be stopped immediately.

The use of drugs of the tetracycline-class during tooth development (second and third trimesters of pregnancy, infancy, and childhood up to the age of 8 years) may cause permanent discoloration of the teeth (yellow-gray-brown). This adverse reaction is more common during long-term use of these drugs, but has been observed following repeated short-term courses. Enamel hypoplasia has also been reported.

All tetracyclines form a stable calcium complex in any bone-forming tissue. A decrease in fibula growth rate has been observed in premature human infants given oral tetracycline in doses of 25 mg/kg every 6 hours. This reaction was shown to be reversible when the drug was discontinued. Results of animal studies indicate that tetracyclines cross the placenta, are found in fetal tissues, and can cause retardation of skeletal development on the developing fetus. Evidence of embryotoxicity has been noted in animals treated with SEYSARA during pregnancy in association with maternal toxicity [see Use in Specific Populations (8.1)].

5.2 Clostridium difficile Associated Diarrhea (Antibiotic Associated Colitis)

Clostridium difficile associated diarrhea (CDAD) has been reported with nearly all antibacterial agents, and may range in severity from mild diarrhea to fatal colitis. Treatment with antibacterial agents alters the normal flora of the colon leading to potential overgrowth of C. difficile.

C. difficile produces toxins A and B which contribute to the development of CDAD. Hypertoxin producing strains of C. difficile cause increased morbidity and mortality, as these infections can be refractory to antimicrobial therapy and may require colectomy. CDAD must be considered in all patients who present with diarrhea following antibiotic use. Careful medical history is necessary since CDAD has been reported to occur over two months after the administration of antibacterial agents.

If CDAD is suspected or confirmed, ongoing antibiotic use not directed against C. difficile should be discontinued. Appropriate fluid and electrolyte management, protein supplementation, antibiotic treatment of C. difficile, and surgical evaluation should be instituted as clinically indicated.

5.3 Central Nervous System Effects

Central nervous system side effects including light-headedness, dizziness or vertigo have been reported with tetracycline use. Patients who experience these symptoms should be cautioned about driving vehicles or using hazardous machinery. These symptoms may disappear during therapy and may disappear when the drug is discontinued.

5.4 Intracranial Hypertension

Intracranial hypertension in adults and adolescents has been associated with the use of tetracyclines. Clinical manifestations include headache, blurred vision and papilledema. Although signs and symptoms of intracranial hypertension resolve after discontinuation of treatment, the possibility for sequelae such as visual loss that may be permanent or severe exists. Women of childbearing age who are overweight have a greater risk for developing intracranial hypertension. Patients should be questioned for visual disturbances prior to initiation of treatment with tetracyclines. Concomitant use of isotretinoin and SEYSARA should be avoided because isotretinoin, a systemic retinoid, is also known to cause intracranial hypertension [see Drug Interactions (7.1)]. If visual disturbance occurs during treatment, patients should be checked for papilledema.

5.5 Photosensitivity

Photosensitivity manifested by an exaggerated sunburn reaction has been observed in some individuals taking tetracyclines. Patients should minimize or avoid exposure to natural or artificial sunlight (tanning beds or UVA/B treatment) while using SEYSARA. If patients need to be outdoors while using SEYSARA, they should wear loose-fitting clothes that protect skin from sun exposure and discuss other sun protection measures with their physician.

5.6 Development of Drug Resistant Bacteria

Bacterial resistance to tetracyclines may develop in patients using SEYSARA. Because of the potential for drug-resistant bacteria to develop during the use of SEYSARA, it should only be used as indicated.

5.7 Superinfection/Potential for Microbial Overgrowth

As with other antibiotic preparations, use of SEYSARA may result in overgrowth of nonsusceptible organisms, including fungi. If superinfection occurs, SEYSARA should be discontinued and appropriate therapy instituted.

6 ADVERSE REACTIONS

6.1 Clinical Trials Experience

Because clinical trials are conducted under widely varying conditions, adverse reaction rates observed in the clinical trials of a drug cannot be directly compared to rates in the clinical trials of another drug and may not reflect the rates observed in practice.

A total of 1064 subjects and 1069 subjects with moderate to severe acne vulgaris were treated with SEYSARA and placebo, respectively, for 12 weeks in 3 controlled clinical trials. The only adverse drug reaction that was reported in at least 1% of subjects was nausea, SEYSARA (3.1%) versus placebo (2.0%).

The following additional adverse drug reactions occurred in less than 1% of female SEYSARA subjects: vulvovaginal mycotic infection (0.8%) and vulvovaginal candidiasis (0.6%).

7 DRUG INTERACTIONS

7.1 Effect of Other Drugs on SEYSARA

Oral Retinoids

Tetracyclines may cause increased intracranial pressure as do oral retinoids, including isotretinoin and acitretin [see Warnings and Precautions (5.4)]. Avoid coadministration of SEYSARA with oral retinoids.

Antacids and Iron Preparations

Coadministration with antacids containing aluminum, calcium or magnesium, bismuth subsalicylate, and iron-containing preparations may impair absorption of SEYSARA, similar to other tetracyclines, which may decrease its efficacy. Separate dosing of SEYSARA from antacids containing aluminum, calcium or magnesium, bismuth subsalicylate, and iron-containing preparations.

7.2 Effect of SEYSARA on Other Drugs

Penicillin

Similar to other tetracyclines, SEYSARA may interfere with the bactericidal action of penicillin. Avoid coadministration of SEYSARA with penicillin.

Anticoagulants

Similar to other tetracyclines, SEYSARA may depress plasma prothrombin activity, which may increase the risk of bleeding in patients who are on anticoagulant therapy. Decrease anticoagulant dosage when coadministered with SEYSARA as appropriate.

P-Glycoprotein (P-gp) Substrates

Concomitant use of SEYSARA may increase concentrations of concomitantly administered P-gp substrates (e.g. digoxin). Monitor for toxicities of drugs that are P-gp substrates and may require dosage reduction when given concurrently with SEYSARA [see Clinical Pharmacology (12.3)].

Oral Hormonal Contraceptives

There is no clinically significant effect of SEYSARA on the efficacy of oral contraceptives containing ethinyl estradiol and norethindrone acetate [see Clinical Pharmacology (12.3)].

8 USE IN SPECIFIC POPULATIONS

8.1 Pregnancy

Risk Summary

SEYSARA, like tetracycline class drugs, may cause fetal harm, permanent discoloration of teeth, and reversible inhibition of bone growth when administered during pregnancy [see Warnings and Precautions (5.1) and Use in Specific Populations (8.4)]. The limited available human data are not sufficient to inform a drug-associated risk for birth defects or miscarriage. Tetracyclines are known to cross the placental barrier; therefore, SEYSARA may be transmitted from the mother to the developing fetus. In animal reproduction studies, sarecycline induced skeletal malformations in fetuses when orally administered to pregnant rats during the period of organogenesis at a dose 1.4 times the maximum recommended human dose (MRHD) of 150 mg/day (based on AUC comparison). When dosing with sarecycline continued through the period of lactation, decreases in offspring survival, offspring body weight, and implantation sites and viable embryos in offspring females occurred at a dose 3 times the MRHD (based on AUC comparison) [see Data]. The potential risk to the fetus outweighs the potential benefit to the mother from SEYSARA use during pregnancy; therefore, pregnant patients should discontinue SEYSARA as soon as pregnancy is recognized.

All pregnancies have a background risk of birth defect, loss, or other adverse outcomes. The background risk of major birth defects and miscarriage for the indicated population is unknown. In the U.S. general population, the estimated background risk of major birth defects and miscarriage in clinically recognized pregnancies is 2% to 4% and 15% to 20%, respectively.

Data

Animal Data

In an embryofetal developmental study in rats, sarecycline was administered to pregnant rats at oral doses up to 500 mg/kg/day during the period of organogenesis. Decreases in maternal body weight, fetal body weight and litter size and increases in the number of resorption and postimplantation loss occurred at 500 mg/kg/day (7 times the MRHD based on AUC comparison). Skeletal malformations (bent forelimb, hindlimb, and scapula) occurred at all dose levels (≥ 50 mg/kg/day, 1.4 times the MRHD based on AUC comparison).

In an embryofetal developmental study in rabbits, sarecycline was administered to pregnant rabbits at oral doses up to 150 mg/kg/day during the period of organogenesis. Excessive maternal toxicity (mortality/moribundity/abortion) occurred at 150 mg/kg/day (5 times the MRHD based on AUC comparison) and this dose group was terminated early. Maternal moribundity also occurred at 100 mg/kg/day (0.6 times the MRHD based on AUC comparison). No significant embryofetal toxicity or malformations were observed at doses up to 100 mg/kg/day (0.6 times the MRHD based on AUC comparison).

In a pre- and post-natal developmental study in rats, sarecycline was administered to maternal rats at oral doses up to 400 mg/kg/day during the period of organogenesis through lactation. Excessive litter toxicity (litter loss and stillbirth) occurred at 400 mg/kg/day (8 times the MRHD based on AUC comparison), which led to early termination of dams at parturition. Decreases in body weight and food consumption of dams during the lactation period occurred at 150 mg/kg/day (3 times the MRHD based on AUC comparison). Decreases in offspring survival and offspring body weight during the preweaning and growth period, and decreases in implantation sites and viable embryos in female offspring occurred at 150 mg/kg/day (3 times the MRHD based on AUC comparison). No significant maternal or developmental toxicity was observed at 50 mg/kg/day (1.4 times the MRHD based on AUC comparison).

8.2 Lactation

Risk Summary

Tetracyclines are excreted in human milk. Because of the potential for serious adverse reactions on bone and tooth development in nursing infants from tetracycline-class antibiotics, advise a woman that breastfeeding is not recommended with SEYSARA therapy [see Warnings and Precautions (5.1)].

8.3 Females and Males of Reproductive Potential

Infertility

Avoid using SEYSARA in males who are attempting to conceive a child. In a fertility study in rats, sarecycline adversely affected spermatogenesis when orally administered to male rats at a dose 8 times the MRHD (based on AUC comparison) [see Nonclinical Toxicology (13.1)].

8.4 Pediatric Use

The safety and effectiveness of SEYSARA have been established in pediatric patients 9 years of age and older for the treatment of moderate to severe inflammatory lesions of non-nodular acne vulgaris [see Pharmacokinetics (12.3) and Clinical Studies (14)].

Safety and effectiveness of SEYSARA in pediatric patients below the age of 9 years has not been established. Use of tetracycline-class antibiotics below the age of 8 is not recommended due to the potential for tooth discoloration [see Warnings and Precautions (5.1)].

8.5 Geriatric Use

Clinical studies of SEYSARA did not include sufficient numbers of subjects aged 65 and over to determine whether they respond differently from younger subjects.

10 OVERDOSAGE

In case of overdosage, discontinue medication, treat symptomatically, and institute supportive measures. Dialysis does not alter serum half-life and thus would not be of benefit in treating cases of overdose.

11 DESCRIPTION

SEYSARA (sarecycline) tablets are a tetracycline class drug for oral administration. Sarecycline hydrochloride is chemically described as (4S,4aS,5aR,12aS)-4-(dimethylamino)-3,10,12,12a-tetrahydroxy-7-[(methoxy-(methyl)-amino)- methyl]-1,11-dioxo-1,4,4a,5,5a,6,11, 12a-octahydrotetracene-2-carboxamide monohydrochloride with an empirical formula of C24H29N3O8.HCl and a molecular weight of 523.96.

The structural formula is represented below:

SEYSARA tablets contain 64.5 mg, 107.5 mg, and 161.2 mg of sarecycline hydrochloride equivalent to 60 mg, 100 mg, and 150 mg sarecycline respectively. Inactive ingredients in the tablet formulations are: microcrystalline cellulose, povidone, sodium starch glycolate, and sodium stearyl fumarate. The yellow film coating contains D&C yellow #10 aluminum lake, iron oxide yellow, methacrylic acid copolymer type C, polyethylene glycol, polyvinyl alcohol, sodium bicarbonate, talc, and titatnium dioxide.

12 CLINICAL PHARMACOLOGY

12.1 Mechanism of Action

Sarecycline is an aminomethylcycline within the tetracycline class of drugs. [see CLINICAL PHARMACOLOGY (12.4)]. The mechanism of action of SEYSARA in treating the inflammatory lesions of non-nodular acne vulgaris is not known.

12.2 Pharmacodynamics

The pharmacodynamics of SEYSARA for the treatment of acne vulgaris are unknown.

Cardiac Electrophysiology

At approximately 3 times the maximum recommended dose, SEYSARA did not prolong the QT interval to a clinically relevant extent.

12.3 Pharmacokinetics

Increasing the SEYSARA dose from 60 to 150 mg once daily in healthy subjects resulted in a slightly less than proportional increase in sarcyeline steady-state Cmax and AUCtau. A mean accumulation ratio of sarecycline ranges from 1.5 to 1.6 fold with repeated dosing. Steady-state of sarecycline was reached by Day 7.

Absorption

The median time to peak plasma concentration (Tmax) of sarecycline is 1.5 to 2.0 hours.

Effect of Food

Coadministration with a high-fat (approximately 50% of total caloric content of the meal), high-calorie (800 to 1000 Kcal) meal that included milk delayed Tmax by approximately 0.53 hour and decreased sarecycline Cmax by 31% and AUC by 27%.

Distribution

Protein binding of sarecycline is 62.5% to 74.7% in vitro. The mean apparent volume of distribution of sarecycline at steady-state ranges from 91.4 L to 97.0 L.

Elimination

The mean apparent oral clearance (CL/F) of sarecycline at steady state is approximately 3 L/h. The mean elimination half-life of sarecycline is 21 to 22 hours.

Metabolism

Metabolism of sarecycline by enzymes in human liver microsomes is minimal (< 15%) in vitro. Minor metabolites resulting from non-enzymic epimerization, O-/N-demethylation, hydroxylation, and desaturation have been found.

Excretion

After a single 100 mg oral dose of radiolabeled sarecycline, 42.6% of the dose was recovered in feces (14.9% as unchanged) and 44.1% in urine (24.7% as unchanged).

Specific Populations

No clinically significant differences in the pharmacokinetics of sarecycline were observed based on age (11 to 73 years), weight (42 to 133 kg), sex, renal impairment, or mild to moderate hepatic impairment (Child Pugh A to B). The effect of end-stage renal disease (ESRD) or severe hepatic impairment (Child-Pugh C) on sarecycline pharmacokinetics has not been assessed.

Drug Interaction Studies

Clinical Studies

Coadministration of SEYSARA with a combination oral contraceptive, ethinyl estradiol (EE) 20 mcg plus norethindrone (NE) acetate 1 mg, increased EE Cmax by 14% and AUCtau by 11%, and increased NE Cmax by 18% and AUCtau by 23%.

Coadministration of a single dose of SEYSARA 150 mg resulted in a 26% increase in Cmax of digoxin, a P-gp substrate.

In Vitro Studies

Sarecycline is not a substrate for P-gp, BCRP, OATP1B1, or OATP1B3.

Sarecycline is a P-gp inhibitor. Sarecycline does not inhibit CYP1A2, CYP2A6, CYP2B6, CYP2C8, CYP2C9, CYP2C19, CYP2D6, CYP2E1, or CYP3A4/5 isozymes, and does not inhibit OATP1B1, OATP1B3, OCT2, OAT1, OAT3, or BCRP.

Sarecycline does not induce CYP1A2, CYP2B6, or CYP3A4/5 isozymes.

12.4 Microbiology

Mechanism of Action
In P. acnes, sarecycline binds to the 30S ribosomal subunit and interacts with 16S ribosomal RNA. Furthermore, it protrudes its C7 moiety into the mRNA binding channel to interact with mRNA. Sarecycline blocks P. acnes protein synthesis and inhibits bacterial growth however, the clinical significance is unknown.

Resistance
P. acnes strains displayed a low propensity for the development of resistance to sarecycline, with spontaneous mutation frequencies being 10^-10 at 4 – 8 × MIC.

Antimicrobial Activity
Sarecycline is active in vitro against most isolates of Propionibacterium acnes.

13 NONCLINICAL TOXICOLOGY

13.1 Carcinogenesis, Mutagenesis, Impairment of Fertility

In a 2-year oral mouse carcinogenicity study and a 2-year oral rat carcinogenicity study, no drug-related neoplasms were observed in male mice at oral doses of sarecycline up to 100 mg/kg/day (approximately equal to the MRHD based on AUC comparison) or in female mice at doses up to 60 mg/kg/day (approximately equal to the MRHD based on AUC comparison), or in rats at doses up to 200/100 mg/kg/day (dose reduced from 200 to 100 mg/kg/day due to increased mortality; 8 times the MRHD based on AUC comparison).

Sarecycline was not mutagenic or clastogenic in a series of in vitro and in vivo genotoxicity studies, including a bacteria reverse mutation (Ames) assay, an in vitro chromosomal aberration assay in CHO cells, the L5178Y/TK+/- Mouse Lymphoma Assay, and an in vivo micronucleus assay in rats.

In a fertility and early embryonic development study in rats, sarecycline was administered to both male and female rats at oral doses up to 400 mg/kg/day prior to pairing and through the mating and postmating period. Female fertility was not affected at doses up to 400 mg/kg/day (8 times the MRHD based on AUC comparison). In sperm evaluation, decreased sperm motility, decreased sperm count and concentration, and an increase in percent abnormal sperm occurred at 400 mg/kg/day (8 times the MRHD based on AUC comparison). Male fertility was not affected at doses up to 150 mg/kg/day (4 times the MRHD based on AUC comparison).

14 CLINICAL STUDIES

The safety and efficacy of once daily SEYSARA was assessed in two 12-week multicenter, randomized, double-blind, placebo-controlled studies (Study 1 [NCT02320149] and Study 2 [NCT02322866]). Efficacy was assessed in a total of 2002 subjects 9 years of age and older. Overall, 57% were female, 78% were Caucasian, 15% were Black or African American and 51% were adults (18 to 45 years of age). Subjects were randomized to receive either SEYSARA or placebo once daily.

The two co-primary efficacy endpoints were:

- Percentage of subjects with Investigator’s Global Assessment (IGA) success: a score of clear (0) or almost clear (1) and 2-point decrease from baseline on IGA score at Week 12.
- Absolute reduction from baseline in inflammatory lesion counts at Week 12.

The results at Week 12 are presented in the following table.

Table 2: Clinical Efficacy of SEYSARA at Week 12
 | Study 1 |  | Study 2
 | SEYSARA (N=483) | Placebo (N=485) | SEYSARA (N=519) | Placebo (N=515)
Investigator’s Global Assessment
IGA Success | 21.9% | 10.5% | 22.6% | 15.3%
Inflammatory Lesions
Mean absolute reduction | 15.3 | 10.2 | 15.5 | 11.1
Mean percent reduction | 52.2% | 35.2% | 50.8% | 36.4%

Mean absolute and percent reduction in inflammatory lesions was also greater with SEYSARA compared to placebo at Weeks 3, 6, and 9 for both studies.

16 HOW SUPPLIED/STORAGE AND HANDLING

How Supplied

1) SEYSARA (sarecycline) tablets, 60 mg are capsule-shaped, yellow, film-coated tablets debossed with “S60” on one side and blank on the other side.
  - Bottles of 30 tablets with child-resistant closure: NDC: 16110-245-30
2) SEYSARA (sarecycline) tablets, 100 mg are capsule-shaped, yellow, film-coated tablets debossed with “S100” on one side and blank on the other side.
  - Bottles of 30 tablets with child-resistant closure: NDC: 16110-246-30
3) SEYSARA (sarecycline) tablets, 150 mg are capsule-shaped, yellow, film-coated tablets debossed with “S150” on one side and blank on the other side.
  - Bottles of 30 tablets with child-resistant closure: NDC: 16110-247-30

Storage

Store at 20°C - 25°C (68°F - 77°F); excursions permitted to 15°C - 30°C (59°F - 86°F) [See USP Controlled Room Temperature].

Handling

Protect from moisture and excessive heat.

17 PATIENT COUNSELING INFORMATION

Advise the patient to read the FDA-approved patient labeling (Patient Information).

Patients taking SEYSARA should receive the following information and instructions:

- SEYSARA should not be used by pregnant women or women attempting to conceive a child [see Use in Specific Populations (8.1)].
- Advise a woman that breastfeeding is not recommended during SEYSARA therapy.
- Advise patients that C. difficile colitis can occur with antibiotic therapy. If patients develop watery or bloody stools, they should seek medical attention.
- Advise patients that intracranial hypertension can occur with tetracycline therapy. If patients experience headache or blurred vision, they should seek medical attention.
- Patients who experience central nervous system symptoms should be cautioned about driving vehicles or using hazardous machinery while on SEYSARA therapy. Patients should seek medical help for persistent central nervous system symptoms.
- Photosensitivity manifested by an exaggerated sunburn reaction has been observed in some individuals taking tetracyclines. Advise patients to minimize or avoid exposure to natural or artificial sunlight (tanning beds or UVA/B treatment) while using SEYSARA. If patients need to be outdoors while using SEYSARA, they should wear loose-fitting clothes that protect skin from sun exposure and discuss other sun protection measures with their physician. Treatment should be discontinued at the first evidence of skin erythema.
- Advise patients that because of the potential for drug-resistant bacteria to develop during the use of SEYSARA, take SEYSARA as directed. Skipping doses or not completing the full course of therapy may decrease the effectiveness of the current treatment course and increase the likelihood that bacteria will develop resistance and will not be treatable by other antibacterial drugs in the future.
- Advise patients to drink fluids liberally along with SEYSARA to reduce the risk of esophageal irritation and ulceration [see Dosage and Administration (2)].

© 2019 Almirall, LLC. All rights reserved.
SEYSARA® is a registered trademark of Almirall, LLC.
Almirall® and its design are trademarks of Almirall, LLC.
Distributed by: Almirall, LLC
Malvern, PA 19355, USA
Almirall

PATIENT INFORMATION

SEYSARA® (SAY' sara)
(sarecycline)
tablets

What is SEYSARA?

- SEYSARA is a prescription medicine used to treat moderate to severe acne vulgaris in people 9 years and older.
- SEYSARA should not be used for the treatment or prevention of infections

It is not known if SEYSARA is safe and effective for use for longer than 12 weeks.
It is not known if SEYSARA is safe and effective in children under 9 years of age.

Do not take SEYSARA:

- if you are allergic to medicines in the tetracycline-class. Ask your healthcare provider or pharmacist for a list of these medicines if you are not sure.

What should I tell my healthcare provider before taking SEYSARA?

Before taking SEYSARA, tell your healthcare provider about all of your medical conditions, including if you:

- have diarrhea or watery stools
- have vision problems
- are pregnant or plan to become pregnant. SEYSARA may harm your unborn baby. Taking SEYSARA during the second and third trimesters of pregnancy may cause serious side effects on the growth of bone and teeth of your baby. Stop taking SEYSARA and call your healthcare provider right away if you become pregnant during your treatment with SEYSARA.
- are breastfeeding or plan to breastfeed. SEYSARA can pass into your breast milk and may harm your baby. Talk to your healthcare provider about the best way to feed your baby if you take SEYSARA. You should not breastfeed during treatment with SEYSARA.

Tell your healthcare provider about all the medicines you take, including prescription and over-the-counter medicines, vitamins, and herbal supplements. SEYSARA and other medicines can affect each other causing serious side effects.

Especially tell your healthcare provider if you take:

- a blood thinner
- a penicillin antibiotic medicine
- antacids that contain aluminum, calcium or magnesium or iron-containing products
- an acne medication taken by mouth that contains isotretinoin or acitretin

How should I take SEYSARA?

- Take SEYSARA exactly as your healthcare provider tells you.
- Skipping doses or not taking all doses of SEYSARA may:
  - make the treatment not work as well.
  - increase the chance that the bacteria will become resistant to SEYSARA.
- Take SEYSARA 1 time a day with or without food.
- Take SEYSARA with enough fluid to completely swallow the tablet and to lower your risk of getting irritation or ulcers in your esophagus. Your esophagus is the tube that connects your mouth to your stomach.
- If you take too much SEYSARA, stop taking SEYSARA and call your healthcare provider right away or go to the nearest hospital emergency room.

What should I avoid during treatment with SEYSARA?

- Avoid sunlight or artificial sunlight, such as a tanning booth or sunlamp. You could get severe sunburn. Use sunscreen and wear loose-fitting clothes that cover your skin while out in sunlight. Stop taking SEYSARA if you get sunburn.
- You should not drive or operate dangerous machinery until you know how SEYSARA affects you. Tetracyclines may cause you to feel dizzy or lightheaded, or have a spinning feeling (vertigo).

What are the possible side effects of SEYSARA?

SEYSARA may cause serious side effects, including:

- Harm to an unborn baby. See “What should I tell my healthcare provider before taking SEYSARA?”
- Permanent teeth discoloration. SEYSARA may permanently turn a baby or child's teeth yellow-gray-brown during tooth development. You should not use SEYSARA during tooth development. Tooth development happens in the second and third trimesters of pregnancy, and from birth to 8 years of age.
- Slow bone growth. SEYSARA may slow bone growth in infants and children. Slow bone growth is reversible after stopping treatment with SEYSARA.
- Diarrhea. Diarrhea can happen with most antibiotics, including SEYSARA. This diarrhea may be caused by an infection (Clostridium difficile) in your intestines. Call your healthcare provider right away if you get watery or bloody stools.
- Central nervous system effects. See “What should I avoid while taking SEYSARA?” Central nervous system effects such as light headedness, dizziness, and a spinning feeling (vertigo) may go away during your treatment with SEYSARA or if treatment is stopped. Call your healthcare provider if these symptoms do not go away.
- Increased pressure around the brain (intracranial hypertension). This condition may lead to vision changes and permanent vision loss. You may be more likely to get intracranial hypertension if you are a female of childbearing potential and are overweight or have a history of intracranial hypertension. Stop taking SEYSARA and tell your healthcare provider right away if you have blurred vision, vision loss, or headaches.
- Sensitivity to sunlight (photosensitivity). See “What should I avoid during treatment with SEYSARA?”

The most common side effect of SEYSARA is nausea.

SEYSARA may cause fertility problems in males. This may affect your ability to father a child. Talk to your healthcare provider if you have concerns about fertility.

These are not all the possible side effects of SEYSARA.

Call your doctor for medical advice about side effects. You may report side effects to FDA at 1-800-FDA-1088. You may also report side effects to Almirall at 1-866-665-2782.

How should I store SEYSARA?

- Store SEYSARA at room temperature between 68°F to 77°F (20°C to 25°C).
- Keep SEYSARA away from moisture and excessive heat.

Keep SEYSARA and all medicines out of the reach of children.

General information about the safe and effective use of SEYSARA.

Medicines are sometimes prescribed for purposes other than those listed in a Patient Information leaflet. Do not use SEYSARA for a condition for which it was not prescribed. Do not give SEYSARA to other people, even if they have the same symptoms that you have. It may harm them. You can ask your healthcare provider or pharmacist for information about SEYSARA that is written for health professionals.

What are the ingredients in SEYSARA?

Active ingredient: sarecycline hydrochloride

Inactive ingredients: microcrystalline cellulose, povidone, sodium starch glycolate, and sodium stearyl fumarate. The yellow film coating contains D&C yellow #10 aluminum lake, iron oxide yellow, methacrylic acid copolymer type C, polyethylene glycol, polyvinyl alcohol, sodium bicarbonate, talc, and titanium dioxide.

© 2019 Almirall, LLC. All rights reserved. ALMIRALL

ALMIRALL

SEYSARA® is a registered trademark of Almirall, LLC.

Almirall® and its design are trademarks of Almirall, LLC.

Distributed by Almirall, LLC

Malvern, PA 19355, USA

This Patient Information has been approved by the U.S. Food and Drug Administration.

Issued: 07/2019